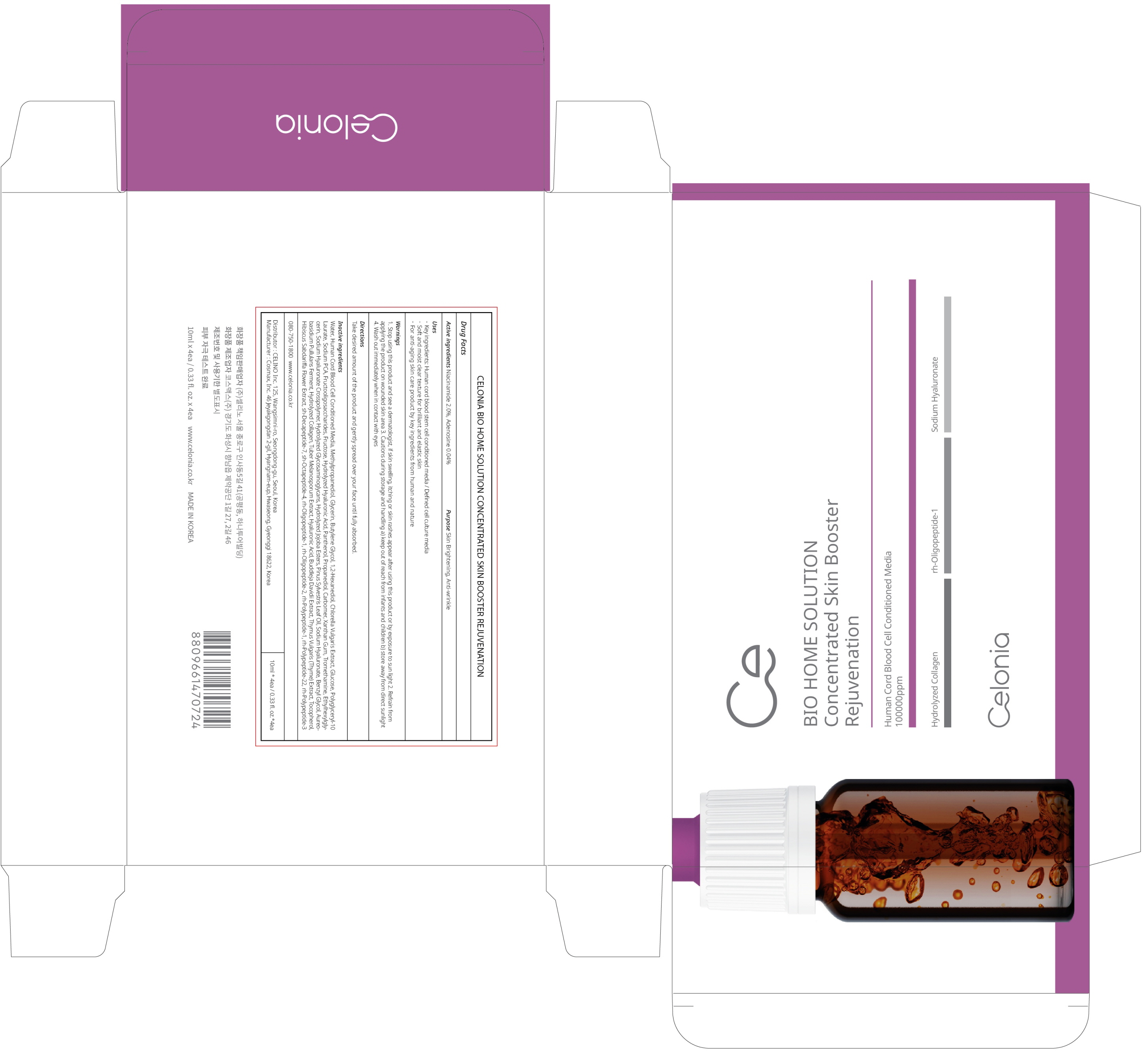 DRUG LABEL: CELONIA BIO HOME SOLUTION CONCENTRATED SKIN BOOSTER REJUVENATION
NDC: 73655-110 | Form: LIQUID
Manufacturer: Celino Inc.
Category: otc | Type: HUMAN OTC DRUG LABEL
Date: 20231115

ACTIVE INGREDIENTS: NIACINAMIDE 0.2 g/10 mL; ADENOSINE 0.004 g/10 mL
INACTIVE INGREDIENTS: Water; Methylpropanediol; Glycerin

ACTIVE INGREDIENTS

NIACINAMIDE 2.0%
ADENOSINE 0.04%

INACTIVE INGREDIENTS

Water, Human Cord Blood Cell Conditioned Media, Methylpropanediol, Glycerin, Butylene Glycol, 1,2-Hexanediol, Chlorella Vulgaris Extract, Glucose, Polyglyceryl-10 Laurate, Sodium PCA, Fructooligosaccharides, Fructose, Hydrolyzed Hyaluronic Acid, Panthenol, Propanediol, Carbomer, Xanthan Gum, Tromethamine, Ethylhexylglycerin, Sodium Hyaluronate Crosspolymer, Hydrolyzed Glycosaminoglycans, Hydrolyzed Jojoba Esters, Pinus Sylvestris Leaf Oil, Sodium Hyaluronate, Benzyl Glycol, Aureobasidium Pullulans Ferment, Hydrolyzed Collagen, Tuber Melanosporum Extract, Hyaluronic Acid, Buddleja Davidii Extract, Thymus Vulgaris (Thyme) Extract, Tocopherol, Hibiscus Sabdariffa Flower Extract, sh-Decapeptide-7, sh-Octapeptide-4, rh-Oligopeptide-1, rh-Oligopeptide-2, rh-Polypeptide-1, rh-Polypeptide-22, rh-Polypeptide-3

PURPOSE

Skin Brightening
Anti wrinkle

WARNINGS

1. Stop using this product and see a dermatologist, if skin swelling, itching or skin rashes appear after using this product or by exposure to sun light 2. Refrain from applying the product on wounded skin area 3. Cautions during storage and handling a) keep out of reach from infants and children b) store away from direct sunlight 4. Wash out immediately when in contact with eyes

KEEP OUT OF REACH OF CHILDREN

keep out of reach from infants and children

Uses

- Key ingredients: Human cord blood stem cell conditioned media / Defined cell culture media
- Soft and moist clear texture for brilliant and elastic skin
- for anti-aging skin care product by key ingredients from human and nature

Directions

Take desired amount of the product and gently spread over your face until fully absorbed.

QUESTIONS

080-750-1800 www.celonia.co.kr